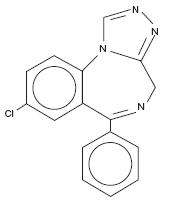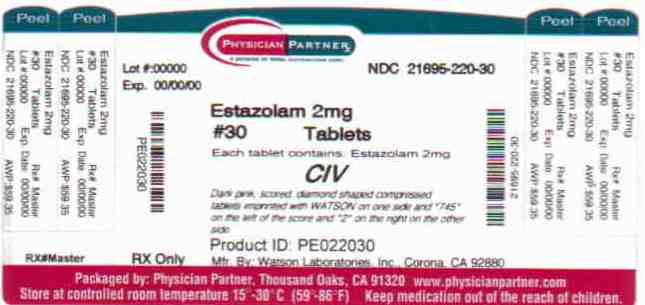 DRUG LABEL: Estazolam
NDC: 21695-220 | Form: TABLET
Manufacturer: Rebel Distributors Corp
Category: prescription | Type: HUMAN PRESCRIPTION DRUG LABEL
Date: 20101220
DEA Schedule: CIV

ACTIVE INGREDIENTS: ESTAZOLAM 2 mg/1 1
INACTIVE INGREDIENTS: DOCUSATE SODIUM; LACTOSE MONOHYDRATE; MAGNESIUM STEARATE; CELLULOSE, MICROCRYSTALLINE; SODIUM BENZOATE; SODIUM STARCH GLYCOLATE TYPE A POTATO; STEARIC ACID; FD&C RED NO. 40; ALUMINUM OXIDE

Estazolam Tablets CIV
Revised: September 2008
Rx only
14444-2

DESCRIPTION

Estazolam, a triazolobenzodiazepine derivative, is an oral hypnotic agent. Estazolam occurs as a fine, white, odorless powder that is soluble in alcohol and practically insoluble in water. The chemical name for estazolam is 8-chloro-6-phenyl-4H-s-triazolo[4,3-α][1,4]benzodiazepine. The molecular formula is C16H11CIN4 and its molecular weight is 294.75. The structural formula is represented as follows:

Each tablet, for oral administration, contains 1 mg or 2 mg estazolam. In addition, each tablet contains the following inactive ingredients: docusate sodium, lactose monohydrate, magnesium stearate, microcrystalline cellulose, sodium benzoate, sodium starch glycolate and stearic acid. The 2 mg tablets also contain FD&C Red #40 aluminum lake.

CLINICAL PHARMACOLOGY

Pharmacokinetics

Absorption

Estazolam tablets have been found to be equivalent in absorption to an orally administered solution of estazolam. In healthy subjects who received up to three times the recommended dose of estazolam, peak estazolam plasma concentrations occurred within two hours after dosing (range 0.5 to 6 hours) and were proportional to the administered dose, suggesting linear pharmacokinetics over the dosage range tested.

Distribution

Independent of concentration, estazolam in plasma is 93% protein bound.

Metabolism

Estazolam is extensively metabolized. Only two metabolites (1-oxo-estazolam and 4-hydroxy-estazolam) were detected in human plasma up to 18 hours.

The pharmacologic activity of estazolam is primarily from the parent drug. The elimination of the parent drug takes place via hepatic metabolism of estazolam to hydroxylated and other metabolites that are eliminated largely in the urine both free and conjugated. In humans, greater than 70% of a single dose of estazolam was recovered in the urine as metabolites. Less than 5% of a 2 mg dose of estazolam was excreted unchanged in the urine, with only 4% of the dose appearing in the feces. The principal urinary excretion product is an unidentified metabolite, presumed to be a metabolic product of 4-hydroxy-estazolam, accounting for at least 27% of the administered dose. 4-hydroxy-estazolam is the major metabolite in plasma, with concentrations approaching 12% of those of the parent eight hours after administration. Urinary 4-hydroxy-estazolam and 1-oxo-estazolam account for 11.9% and 4.4% of the dose respectively. In vitro studies with human liver microsomes indicate that the biotransformation of estazolam to the major circulating metabolite 4-hydroxy-estazolam is mediated by cytochrome P450 3A (CYP3A). While 4-hydroxy-estazolam and the lesser metabolite, 1-oxo-estazolam, have some pharmacologic activity, their low potencies and low concentrations preclude any significant contribution to the hypnotic effect of estazolam.

Elimination

The range of estimates for the mean elimination half-life of estazolam varied from 10 to 24 hours. Radiolabel mass balance studies indicate that the main route of excretion is via the kidneys. After 5 days, 87% of the administered radioactivity was excreted in human urine. Less than 4% of the dose was excreted unchanged. Eleven metabolites were found in urine. Four metabolites were identified as 1-oxo-estazolam, 4’-hydroxy-estazolam, 4-hydroxy-estazolam, and benzophenone, as free metabolites or glucuronides. The predominant metabolite in urine (17% of the administered dose) has not been identified, but is likely to be a metabolite of 4-hydroxy-estazolam.

Special Populations

In a small study (N=8) using various doses in older subjects (59 to 68 years), peak estazolam concentrations were found to be similar to those observed in younger subjects with a mean elimination half-life of 18.4 hours (range 13.5 to 34.6 hours). The influence of hepatic or renal impairment on the pharmacokinetics of estazolam has not been studied.

Pediatrics: The pharmacokinetics of estazolam have not been studied in pediatric patients.

Race: The influence of race on the pharmacokinetics of estazolam has not been studied.

Gender: The gender-effect on the pharmacokinetics of estazolam has not been investigated.

Cigarette Smoking: The clearance of benzodiazepines is accelerated in smokers compared to nonsmokers, and there is evidence that this occurs with estazolam. This decrease in half-life, presumably due to enzyme induction by smoking, is consistent with other drugs with similar hepatic clearance characteristics. In all subjects and at all doses, the mean elimination half-life appeared to be independent of the dose.

Drug-Drug Interaction: The metabolism of estazolam to the major circulating metabolite 4-hydroxy-estazolam is catalyzed by CYP3A. While no in vivo drug-drug interaction studies were conducted between estazolam and inhibitors/inducers of CYP3A, compounds that are potent CYP3A inhibitors (such as ketoconazole, itraconazole, nefazodone, fluvoxamine, and erythromycin) would be expected to increase plasma estazolam concentrations and CYP3A inducers (such as carbamazepine, phenytoin, rifampin and barbiturates) would be expected to decrease estazolam concentrations.

Drug Interaction with Fluoxetine: A multiple-dose study was conducted to assess the effect of fluoxetine 20 mg BID on the pharmacokinetics of estazolam 2 mg QHS after seven days. The pharmacokinetics of estazolam (Cmax and AUC) were not affected during multiple-dose fluoxetine, suggesting no clinically significant pharmacokinetic interaction.

The Ability of Estazolam to Induce or Inhibit Human Enzyme Systems: The results from in vitro human liver microsomal studies suggest that at therapeutic concentrations, estazolam has no significant inhibitory effect on the major human cytochrome P450 enzyme activities (i.e., CYP1A2, CYP2A6, CYP2C9, CYP2C19, CYP2D6, CYP2E1, and CYP3A). The ability of estazolam to induce human hepatic enzyme systems has not been determined.

Pharmacodynamics

Postulated relationship between elimination rate of benzodiazepine hypnotics and their profile of common untoward effects: The type and duration of hypnotic effects and the profile of unwanted effects during administration of benzodiazepine drugs may be influenced by the biologic half-life of administered drug and any active metabolites formed. If half-lives are long, drug or metabolites may accumulate during periods of nightly administration and may be associated with impairments of cognitive and/or motor performance during waking hours; the possibility of interaction with other psychoactive drugs or alcohol will be increased. In contrast, if half-lives are short, drug and metabolites will be cleared before the next dose is ingested, and carry-over effects related to excessive sedation or CNS depression should be minimal or absent. However, during nightly use for an extended period, pharmacodynamic tolerance or adaptation to some effects of benzodiazepine hypnotics may develop. If the drug has a short elimination half-life, it is possible that a relative deficiency of the drug or its active metabolites (i.e., in relationship to the receptor site) may occur at some point in the interval between each night’s use. This sequence of events may account for two clinical findings reported to occur after several weeks of nightly use of rapidly eliminated benzodiazepine hypnotics, namely, increased wakefulness during the last third of the night and increased daytime anxiety in selected patients.

CLINICAL STUDIES

Controlled Trials Supporting Efficacy: In three 7-night, double-blind, parallel-group trials comparing estazolam 1 mg and/or 2 mg with placebo in adult outpatients with chronic insomnia, estazolam 2 mg was consistently superior to placebo in subjective measures of sleep induction (latency) and sleep maintenance (duration, number of awakenings, depth and quality of sleep); estazolam 1 mg was similarly superior to placebo on all measures of sleep maintenance, however, it significantly improved sleep induction in only one of two studies. In a similarly designed trial comparing estazolam 0.5 mg and 1 mg with placebo in geriatric outpatients with chronic insomnia, only the 1 mg estazolam dose was consistently superior to placebo in sleep induction (latency) and in only one measure of sleep maintenance (i.e., duration of sleep).

In a single-night, double-blind, parallel-group trial comparing estazolam 2 mg and placebo in patients admitted for elective surgery and requiring sleep medications, estazolam was superior to placebo in subjective measures of sleep induction and maintenance.

In a 12-week, double-blind, parallel-group trial including a comparison of estazolam 2 mg and placebo in adult outpatients with chronic insomnia, estazolam was superior to placebo in subjective measures of sleep induction (latency) and maintenance (duration, number of awakenings, total wake time during sleep) at week 2, but produced consistent improvement over 12 weeks only for sleep duration and total wake time during sleep. Following withdrawal at week 12, rebound insomnia was seen at the first withdrawal week, but there was no difference between drug and placebo by the second withdrawal week in all parameters except latency, for which normalization did not occur until the fourth withdrawal week.

Adult outpatients with chronic insomnia were evaluated in a sleep laboratory trial comparing four doses of estazolam (0.25, 0.5, 1 and 2 mg) and placebo, each administered for 2 nights in a crossover design. The higher estazolam doses were superior to placebo in most EEG measures of sleep induction and maintenance, especially at the 2 mg dose, but only for sleep duration in subjective measures of sleep.

INDICATIONS AND USAGE

Estazolam tablets are indicated for the short-term management of insomnia characterized by difficulty in falling asleep, frequent nocturnal awakenings, and/or early morning awakenings. Both out-patient studies and a sleep laboratory study have shown that estazolam administered at bedtime improved sleep induction and sleep maintenance (see CLINICAL PHARMACOLOGY).

Because insomnia is often transient and intermittent, the prolonged administration of estazolam is generally neither necessary nor recommended. Since insomnia may be a symptom of several other disorders, the possibility that the complaint may be related to a condition for which there is a more specific treatment should be considered.

There is evidence to support the ability of estazolam to enhance the duration and quality of sleep for intervals up to 12 weeks (see CLINICAL PHARMACOLOGY).

CONTRAINDICATIONS

Benzodiazepines may cause fetal damage when administered during pregnancy. An increased risk of congenital malformations associated with the use of diazepam and chlordiazepoxide during the first trimester of pregnancy has been suggested in several studies. Transplacental distribution has resulted in neonatal CNS depression and also withdrawal phenomena following the ingestion of therapeutic doses of a benzodiazepine hypnotic during the last weeks of pregnancy.

Estazolam is contraindicated in pregnant women. If there is a likelihood of the patient becoming pregnant while receiving estazolam she should be warned of the potential risk to the fetus and instructed to discontinue the drug prior to becoming pregnant. The possibility that a woman of childbearing potential is pregnant at the time of institution of therapy should be considered.

Estazolam is contraindicated with ketoconazole and itraconazole, since these medications significantly impair oxidative metabolism mediated by CYP3A (see WARNINGS and PRECAUTIONS: Drug Interactions).

WARNINGS

Because sleep disturbances may be presenting manifestations of a physical and/or psychiatric disorder, symptomatic treatment of insomnia should be initiated only after a careful evaluation of the patient. The failure of insomnia to remit after 7 to 10 days of treatment may indicate the presence of a primary psychiatric and/or medical illness that should be evaluated. Worsening of insomnia or the emergence of new thinking or behavior abnormalities may be the consequence of an unrecognized psychiatric or physical disorder. Such findings have emerged during the course of treatment with sedative-hypnotic drugs. Because some of the important adverse effects of sedative-hypnotics appear to be dose related (see PRECAUTIONS and DOSAGE AND ADMINISTRATION), it is important to use the smallest possible effective dose, especially in the elderly.

Complex behaviors such as “sleep driving” (i.e., driving while not fully awake after ingestion of a sedative-hypnotic, with amnesia for the event) have been reported. These events can occur in sedative-hypnotic-naïve as well as in sedative-hypnotic-experienced persons. Although behaviors such as sleep-driving may occur with sedative-hypnotics alone at therapeutic doses, the use of alcohol and other CNS depressants with sedative-hypnotics appears to increase the risk of such behaviors, as does the use of sedative-hypnotics at doses exceeding the maximum recommended dose. Due to the risk to the patient and community, discontinuation of sedative-hypnotics should be strongly considered for patients who report a “sleep-driving” episode.

Other complex behaviors (e.g., preparing and eating food, making phone calls, or having sex) have been reported in patients who are not fully awake after taking a sedativehypnotic. As with sleep-driving, patients usually do not remember these events.

Severe anaphylactic and anaphylactoid reactions

Rare cases of angioedema involving the tongue, glottis or larynx have been reported in patients after taking the first or subsequent doses of sedative-hypnotics, including Estazolam. Some patients have had additional symptoms such as dyspnea, throat closing, or nausea and vomiting that suggest anaphylaxis. Some patients have required medical therapy in the emergency department. If angioedema involves the tongue, glottis or larynx, airway obstruction may occur and be fatal. Patients who develop angioedema after treatment with Estazolam should not be rechallenged with the drug.

Estazolam, like other benzodiazepines, has CNS depressant effects. For this reason, patients should be cautioned against engaging in hazardous occupations requiring complete mental alertness, such as operating machinery or driving a motor vehicle, after ingesting the drug, including potential impairment of the performance of such activities that may occur the day following ingestion of estazolam. Patients should also be cautioned about possible combined effects with alcohol and other CNS depressant drugs.

As with all benzodiazepines, amnesia, paradoxical reactions (e.g., excitement, agitation, etc.), and other adverse behavioral effects may occur unpredictably.

There have been reports of withdrawal signs and symptoms of the type associated with withdrawal from CNS depressant drugs following the rapid decrease or the abrupt discontinuation of benzodiazepines (see DRUG ABUSE AND DEPENDENCE).

Estazolam Interaction with Drugs that Inhibit Metabolism via Cytochrome P450 3A (CYP3A): The metabolism of estazolam to the major circulating metabolite 4-hydroxy-estazolam and the metabolism of other triazolobenzodiazepines is catalyzed by CYP3A. Consequently, estazolam should be avoided in patients receiving ketoconazole and itraconazole, which are very potent inhibitors of CYP3A (see CONTRAINDICATIONS). With drugs inhibiting CYP3A to a lesser, but still significant degree, estazolam should be used only with caution and consideration of appropriate dosage reduction. The following are examples of drugs known to inhibit the metabolism of other related benzodiazepines, presumably through inhibition of CYP3A: nefazodone, fluvoxamine, cimetidine, diltiazem, isoniazide, and some macrolide antibiotics.

While no in vivo drug-drug interaction studies were conducted between estazolam and inducers of CYP3A, compounds that are potent CYP3A inducers (such as carbamazepine, phenytoin, rifampin, and barbiturates) would be expected to decrease estazolam concentrations.

PRECAUTIONS

General

Impaired motor and/or cognitive performance attributable to the accumulation of benzodiazepines and their active metabolites following several days of repeated use at their recommended doses is a concern in certain vulnerable patients (e.g., those especially sensitive to the effects of benzodiazepines or those with a reduced capacity to metabolize and eliminate them) [see DOSAGE AND ADMINISTRATION].

Elderly or debilitated patients and those with impaired renal or hepatic function should be cautioned about these risks and advised to monitor themselves for signs of excessive sedation or impaired conditions.

Estazolam appears to cause dose-related respiratory depression that is ordinarily not clinically relevant at recommended doses in patients with normal respiratory function. However, patients with compromised respiratory function may be at risk and should be monitored appropriately. As a class, benzodiazepines have the capacity to depress respiratory drive; there are insufficient data available, however, to characterize their relative potency in depressing respiratory drive at clinically recommended doses.

As with other benzodiazepines, estazolam should be administered with caution to patients exhibiting signs or symptoms of depression. Suicidal tendencies may be present in such patients and protective measures may be required. Intentional overdosage is more common in this group of patients; therefore, the least amount of drug that is feasible should be prescribed for the patient at any one time.

Information for Patients

“Sleep-Driving” and other complex behaviors:

There have been reports of people getting out of bed after taking a sedative-hypnotic and driving their cars while not fully awake, often with no memory of the event. If a patient experiences such an episode, it should be reported to his or her doctor immediately, since “sleep-driving” can be dangerous. This behavior is more likely to occur when sedativehypnotics are taken with alcohol or other central nervous system depressants (see WARNINGS). Other complex behaviors (e.g., preparing and eating food, making phone calls, or having sex) have been reported in patients who are not fully awake after taking a sedativehypnotic. As with sleep-driving, patients usually do not remember these events.

To assure the safe and effective use of estazolam, the following information and instructions should be given to patients:

1. Inform your physician about any alcohol consumption and medicine you are taking now, including drugs you may buy without a prescription. Alcohol should not be used during treatment with hypnotics.
2. Inform your physician if you are planning to become pregnant, if you are pregnant, or if you become pregnant while you are taking this medicine.
3. You should not take this medicine if you are nursing, as the drug may be excreted in breast milk.
4. Until you experience the way this medicine affects you, do not drive a car, operate potentially dangerous machinery, or engage in hazardous occupations requiring complete mental alertness after taking this medicine.
5. Since benzodiazepines may produce psychological and physical dependence, you should not increase the dose before consulting your physician. In addition, since the abrupt discontinuation of estazolam may be associated with temporary sleep disturbances, you should consult your physician before abruptly discontinuing doses of 2 mg per night or more.

Laboratory Tests

Laboratory tests are not ordinarily required in otherwise healthy patients. When treatment with estazolam is protracted, periodic blood counts, urinalyses, and blood chemistry analyses are advisable.

Drug Interactions

If estazolam is given concomitantly with other drugs acting on the central nervous system, careful consideration should be given to the pharmacology of all agents. The action of the benzodiazepines may be potentiated by anticonvulsants, antihistamines, alcohol, barbiturates, monoamine oxidase inhibitors, narcotics, phenothiazines, psychotropic medications, or other drugs that produce CNS depression. Smokers have an increased clearance of benzodiazepines as compared to nonsmokers; this was seen in studies with estazolam (see CLINICAL PHARMACOLOGY).

While no in vivo drug-drug interaction studies were conducted between estazolam and inducers of CYP3A, compounds that are potent CYP3A inducers (such as carbamazepine, phenytoin, rifampin, and barbiturates) would be expected to decrease estazolam concentrations.

Estazolam Interaction with Drugs that Inhibit Metabolism via Cytochrome P450 3A (CYP3A):

The metabolism of estazolam to the major circulating metabolite 4-hydroxy-estazolam and the metabolism of other triazolobenzodiazepines is catalyzed by CYP3A. Consequently, estazolam should be avoided in patients receiving ketoconazole and itraconazole, which are very potent inhibitors of CYP3A (see CONTRAINDICATIONS). With drugs inhibiting CYP3A to a lesser, but still significant degree, estazolam should be used only with caution and consideration of appropriate dosage reduction. The following are examples of drugs known to inhibit the metabolism of other related benzodiazepines, presumably through inhibition of CYP3A: nefazodone, fluvoxamine, cimetidine, diltiazem, isoniazide, and some macrolide antibiotics.

Drug Interaction with Fluoxetine: A multiple-dose study was conducted to assess the effect of fluoxetine 20 mg BID on the pharmacokinetics of estazolam 2 mg QHS after seven days. The pharmacokinetics of estazolam (Cmax and AUC) were not affected during multiple-dose fluoxetine, suggesting no clinically significant pharmacokinetic interaction.

Estazolam Interaction with Other Drugs that are Metabolized by Cytochrome P450 (CYP): At clinically relevant concentrations, in vitro studies indicate that estazolam (0.6μM) was not inhibitory towards the major cytochrome P450 isoforms CYP1A2, CYP2A6, CYP2C9, CYP2C19, CYP2D6, CYP2E1, and CYP3A. Therefore, based on these in vitro data, estazolam is very unlikely to inhibit the biotransformation of other drugs metabolized by these CYP isoforms.

Carcinogenesis, Mutagenesis, Impairment of Fertility

Two-year carcinogenicity studies were conducted in mice and rats at dietary doses of 0.8, 3 and 10 mg/kg/day and 0.5, 2, and 10 mg/kg/day, respectively. Evidence of tumorigenicity was not observed in either study. Incidence of hyperplastic liver nodules increased in female mice given the mid- and high-dose levels. The significance of such nodules in mice is not known at this time.

In vitro and in vivo mutagenicity tests including the Ames test, DNA repair in B. subtilis, in vivo cytogenetics in mice and rats, and the dominant lethal test in mice did not show a mutagenic potential for estazolam.

Fertility in male and female rats was not affected by doses up to 30 times the usual recommended human dose.

Pregnancy

1.Teratogenic Effects

Pregnancy Category X (see CONTRAINDICATIONS).

2.Nonteratogenic Effects

Nonteratogenic Effects: The child born of a mother taking benzodiazepines may be at some risk for withdrawal symptoms during the postnatal period. Neonatal flaccidity has been reported in an infant born of a mother who received benzodiazepines during pregnancy.

Labor and Delivery

Estazolam has no established use in labor or delivery.

Nursing Mothers

Human studies have not been conducted; however, studies in lactating rats indicate that estazolam and/or its metabolites are secreted in the milk. The use of estazolam in nursing mothers is not recommended.

Pediatric Use

Safety and effectiveness in pediatric patients below the age of 18 have not been established.

Geriatric Use

Approximately 18% of individuals participating in the premarketing clinical trials of estazolam were 60 years of age or older. Overall, the adverse event profile did not differ substantively from that observed in younger individuals. Care should be exercised when prescribing benzodiazepines to small or debilitated elderly patients (see DOSAGE AND ADMINISTRATION).

ADVERSE REACTIONS

Commonly Observed: The most commonly observed adverse events associated with the use of estazolam, not seen at an equivalent incidence amoung placebo-treated patients were somnolence, hypokinesia, dizziness, and abnormal coordination.

Associated with Discontinuation of Treatment: Approximately 3% of 1277 patients who received estazolam in US premarketing clinical trials discontinued treatment because of an adverse clinical event. The only event commonly associated with discontinuation, accounting for 1.3% of the total, was somnolence.

Incidence in Controlled Clinical Trials: The table below enumerates adverse events that occurred at an incidence of 1% or greater among patients with insomnia who received estazolam in 7-night, placebo-controlled trials. Events reported by investigators were classified into standard dictionary (COSTART) terms to establish event frequencies. Event frequencies reported were not corrected for the occurrence of these events at baseline. The frequencies were obtained from data pooled across six studies: Estazolam, N=685; placebo, N=433. The prescriber should be aware that these figures cannot be used to predict the incidence of side effects in the course of usual medical practice in which patient characteristics and other factors differ from those that prevailed in these six clinical trials. Similarly, the cited frequencies cannot be compared with figures obtained from other clinical investigators involving related drug products and uses, since each group of drug trials was conducted under a different set of conditions. However, the cited figures provide the physician with a basis of estimating the relative contribution of drug and nondrug factors to the incidence of side effects in the population studied.

INCIDENCE OF ADVERSE EXPERIENCES IN PLACEBO-CONTROLLED CLINICAL TRIALS
(Percentage of Patients Reporting)
 | Estazolam | Placebo
Body System/Adverse Event* | (N=685) | (N=433)
Body as a Whole
Headache | 16 | 27
Asthenia | 11 | 8
Malaise | 5 | 5
Lower extremity pain | 3 | 2
Back pain | 2 | 2
Body pain | 2 | 2
Abdominal pain | 1 | 2
Chest pain | 1 | 1
Digestive System
Nausea | 4 | 5
Dyspepsia | 2 | 2
Musculoskeletal System
Stiffness | 1 | --
Nervous System
Somnolence | 42 | 27
Hypokinesia | 8 | 4
Nervousness | 8 | 11
Dizziness | 7 | 3
Coordination abnormal | 4 | 1
Hangover | 3 | 2
Confusion | 2 | --
Depression | 2 | 3
Dream abnormal | 2 | 2
Thinking abnormal | 2 | 1
Respiratory System
Cold symptoms | 3 | 5
Pharyngitis | 1 | 2
Skin and Appendages
Pruritus | 1 | --
* Events reported by at least 1% of estazolam patients.

Other Adverse Events:

During clinical trials, some of which were not placebo-controlled, estazolam was administered to approximately 1300 patients. Untoward events associated with this exposure were recorded by clinical investigators using terminology of their own choosing. To provide a meaningful estimate of the proportion of individuals experiencing adverse events, similar types of untoward events must be grouped into a smaller number of standardized event categories. In the tabulations that follow, a standard COSTART dictionary terminology has been used to classify reported adverse events. The frequencies presented, therefore, represent the proportion of the 1277 individuals exposed to estazolam who experienced an event of the type cited on at least one occasion while receiving estazolam. All reported events are included except those already listed in the previous table, those COSTART terms too general to be informative, and those events where a drug cause was remote. Events are further classified within body system categories and enumerated in order of decreasing frequency using the following definitions: frequent adverse events are defined as those occurring on one or more occasions in at least 1/100 patients; infrequent adverse events are those occurring in 1/100 to 1/1000 patients; rare events are those occurring in less than 1/1000 patients. It is important to emphasize that, although the events reported did occur during treatment with estazolam, they were not necessarily caused by it.

Body as a Whole - Infrequent: allergic reaction, chills, fever, neck pain, upper extremity pain; Rare: edema, jaw pain, swollen breast.

Cardiovascular System- Infrequent: flushing, palpitation; Rare: arrhythmia, syncope.

Digestive System- Frequent: constipation, dry mouth; Infrequent: decreased appetite, flatulence, gastritis, increased appetite, vomiting; Rare: enterocolitis, melena, ulceration of the mouth.

Endocrine System- Rare: thyroid nodule.

Hematologic and Lymphatic System- Rare: leukopenia, purpura, swollen lymph nodes.

Metabolic/Nutritional Disorders- Infrequent: thirst; Rare: increased SGOT, weight gain, weight loss.

Musculoskeletal System- Infrequent: arthritis, muscle spasm, myalgia; Rare: arthralgia.

Nervous System- Frequent: anxiety; Infrequent: agitation, amnesia, apathy, emotional lability, euphoria, hostility, paresthesia, seizure, sleep disorder, stupor, twitch; Rare: ataxia, circumoral paresthesia, decreased libido, decreased reflexes, hallucinations, neuritis, nystagmus, tremor. Minor changes in EEG patterns, usually low-voltage fast activity, have been observed in patients during estazolam therapy or withdrawal and are of no known clinical significance.

Respiratory System- Infrequent: asthma, cough, dyspnea, rhinitis, sinusitis; Rare: epistaxis, hyperventilation, laryngitis.

Skin and Appendages- Infrequent: rash, sweating, urticaria; Rare: acne, dry skin.

Special Senses- Infrequent: abnormal vision, ear pain, eye irritation, eye pain, eye swelling, perverse taste, photophobia, tinnitus; Rare: decreased hearing, diplopia, scotomata.

Urogenital System- Infrequent: frequent urination, menstrual cramps, urinary hesitancy, urinary urgency, vaginal discharge/itching; Rare: hematuria, nocturia, oliguria, penile discharge, urinary incontinence.

Postintroduction Reports- Voluntary reports of non-US postmarketing experience with estazolam have included rare occurrences of photosensitivity, Stevens-Johnson syndrome, and agranulocytosis. Because of the uncontrolled nature of these spontaneous reports, a causal relationship to estazolam treatment has not been determined.

DRUG ABUSE AND DEPENDENCE

Controlled Substance

Estazolam tablets are a controlled substance in Schedule IV.

Abuse and Dependence

Abuse and addiction are separate and distinct from physical dependence and tolerance. Abuse is characterized by misuse of the drug for non-medical purposes, often in combination with other psychoactive substances. Physical dependence is a state of adaptation that is manifested by a specific withdrawal syndrome that can be produced by abrupt cessation, rapid dose reduction, decreasing blood level of the drug and/or administration of an antagonist. Tolerance is a state of adaptation in which exposure to a drug induces changes that result in a diminution of one or more of the drug’s effects over time. Tolerance may occur to both the desired and undesired effects of drugs and may develop at different rates for different effects.

Addiction is a primary, chronic, neurobiological disease with genetic, psychosocial, and environmental factors influencing its development and manifestations. It is characterized by behaviors that include one or more of the following: impaired control over drug use, compulsive use, continued use despite harm, and craving. Drug addiction is a treatable disease, utilizing a multidisciplinary approach, but relapse is common.

Withdrawal symptoms similar to those noted with sedatives/hypnotics and alcohol have occurred following the abrupt discontinuation of drugs in the benzodiazepine class. The symptoms can range from mild dysphoria and insomnia to a major syndrome that may include abdominal and muscle cramps, vomiting, sweating, tremors, and convulsions.

Although withdrawal symptoms are more commonly noted after the discontinuation of higher than therapeutic doses of benzodiazepines, a proportion of patients taking benzodiazepines chronically at therapeutic doses may become physically dependent on them. Available data, however, cannot provide a reliable estimate of the incidence of dependency or the relationship of the dependency to dose and duration of treatment. There is some evidence to suggest that gradual reduction of dosage will attenuate or eliminate some withdrawal phenomena. In most instances, withdrawal phenomena are relatively mild and transient; however, life-threatening events (e.g., seizures, delirium, etc.) have been reported.

Gradual withdrawal is the preferred course for any patient taking benzodiazepines for a prolonged period. Patients with a history of seizures, regardless of their concomitant antiseizure drug therapy, should not be withdrawn abruptly from benzodiazepines.

Individuals with a history of addiction to or abuse of drugs or alcohol should be under careful surveillance when receiving benzodiazepines because of the risk of habituation and dependence to such patients.

OVERDOSAGE

As with other benzodiazepines, experience with estazolam indicates that manifestations of overdosage include somnolence, respiratory depression, confusion, impaired coordination, slurred speech, and ultimately, coma. Patients have recovered from overdosage as high as 40 mg. As in the management of intentional overdose with any drug, the possibility should be considered that multiple agents may have been taken.

Gastric evacuation, either by the induction of emesis, lavage, or both, should be performed immediately. Maintenance of adequate ventilation is essential. General supportive care, including frequent monitoring of the vital signs and close observation of the patient, is indicated. Fluids should be administered intravenously to maintain blood pressure and encourage diuresis. The value of dialysis in treatment of benzodiazepine overdose has not been determined. The physician may wish to consider contacting a Poison Control Center for up-to-date information on the management of hypnotic drug product overdose.

Flumazenil, a specific benzodiazepine receptor antagonist, is indicated for the complete or partial reversal of the sedative effects of benzodiazepines and may be used in situations when an overdose with a benzodiazepine is known or suspected. Prior to the administration of flumazenil, necessary measures should be instituted to secure airway, ventilation, and intravenous access. Flumazenil is intended as an adjunct to, not as a substitute for, proper management of benzodiazepine overdose. Patients treated with flumazenil should be monitored for resedation, respiratory depression, and other residual benzodiazepine effects for an appropriate period after treatment. The prescriber should be aware of a risk of seizure in association with flumazenil treatment, particularly in long-term benzodiazepine users and in cyclic antidepressant overdose. The complete flumazenil package insert including CONTRAINDICATIONS, WARNINGS, and PRECAUTIONS should be consulted prior to use.

DOSAGE AND ADMINISTRATION

The recommended initial dose for adults is 1 mg at bedtime; however, some patients may need a 2 mg dose. In healthy elderly patients, 1 mg is also the appropriate starting dose, but increases should be initiated with particular care. In small or debilitated older patients, a starting dose of 0.5 mg, while only marginally effective in the overall elderly population, should be considered.

HOW SUPPLIED

Estazolam Tablets, 2 mg are dark pink, scored, diamond shaped compressed tablets imprinted with WATSON on one side of the tablet and on the other side with 745 on the left side of the score and 2 on the right side of the score, supplied in bottles of 30.

Store at 20°-25°C (68°-77°F). [See USP controlled room temperature.]

Dispense in a tight, light-resistant container as defined in the USP.

Manufactured By:
Watson Laboratories, Inc.
Corona, CA 92880 USA

Distributed By:
Watson Pharma, Inc.
Corona, CA 92880 USA

Repackaged by:

Rebel Distributors Corp

Thousand Oaks, CA 91320

MEDICATION GUIDE

SEDATIVE-HYPNOTIC TABLETS/CAPSULES C-IV

Read this Medication Guide before you start taking a SEDATIVE-HYPNOTIC and each time you get a refill. There may be new information. This Medication Guide does not take the place of talking to your doctor about your medical condition or treatment. You and your doctor should talk about the SEDATIVE-HYPNOTIC when you start taking it and at regular checkups.

What is the most important information I should know about SEDATIVE HYPNOTICS?

After taking a SEDATIVE-HYPNOTIC, you may get up out of bed while not being fully awake and do an activity that you do not know you are doing. The next morning, you may not remember that you did anything during the night. You have a higher chance of doing these activities if you drink alcohol or take other medicines that make you sleepy with a SEDATIVE-HYPNOTIC. Reported activities include:

- driving a car (“sleep driving”)
- making and eating food
- talking on the phone
- having sex
- sleep-walking

Important:

1. Take SEDATIVE-HYPNOTICS exactly as prescribed
  Do not take more SEDATIVE-HYPNOTICS than prescribed.
  Take the SEDATIVE-HYPNOTIC right before you get in bed, not sooner.
2. Do not take SEDATIVE-HYPNOTICS if you:
  - drink alcohol
  - take other medicines that can make you sleepy. Talk to your doctor about all of your medicines. Your doctor will tell you if you can take SEDATIVE-HYPNOTICS with your other medicines
  - cannot get a full night’s sleep
  Call your doctor right away if you find out that you have done any of the above activities after taking the SEDATIVE-HYPNOTIC.

What are SEDATIVE-HYPNOTICS?

SEDATIVE-HYPNOTICS are sleep medicines. SEDATIVE-HYPNOTICS are used in adults for the short-term treatment of the symptom of trouble falling asleep from insomnia. SEDATIVE-HYPNOTICS do not treat other symptoms of insomnia which include waking up too early in the morning and waking up often during the night.

SEDATIVE-HYPNOTICS are not for children.

BOXED WARNING

SEDATIVE-HYPNOTICS are federally controlled substances (C-IV) because they can be abused or lead to dependence. Keep SEDATIVE-HYPNOTICS in a safe place to prevent misuse and abuse. Selling or giving away SEDATIVE-HYPNOTICS may harm others, and is against the law. Tell your doctor if you have ever abused or been dependent on alcohol, prescription medicines or street drugs.

Who should not take SEDATIVE-HYPNOTICS?

Do not take SEDATIVE-HYPNOTICS if you are allergic to anything in it. See the end of this Medication Guide for a complete list of ingredients in Estazolam Tablets.

SEDATIVE-HYPNOTICS may not be right for you. Before starting SEDATIVE-HYPNOTICS, tell your doctor about all of your health conditions, including if you:

- have a history of depression, mental illness, or suicidal thoughts
- have a history of drug or alcohol abuse or addiction
- have kidney or liver disease
- have a lung disease or breathing problems
- are pregnant, planning to become pregnant, or breastfeeding

Tell your doctor about all of the medicines you take including prescription and nonprescription medicines, vitamins and herbal supplements. Medicines can interact, sometimes causing side effects. Do not take SEDATIVE-HYPNOTICS with other medicines that can make you sleepy.

Know the medicines that you take. Keep a list of your medicines with you to show your doctor and pharmacist each time you get a new medicine.

How should I take SEDATIVE-HYPNOTICS?

- Take SEDATIVE-HYPNOTICS exactly as prescribed. Do not take more SEDATIVE-HYPNOTIC than prescribed for you.
- Take SEDATIVE-HYPNOTICS right before you get into bed. Or you can take the SEDATIVE-HYPNOTIC after you have been in bed and have trouble falling asleep.
- Do not take SEDATIVE-HYPNOTICS with or right after a meal.
- Do not take SEDATIVE-HYPNOTICS unless you are able to get a full night’s sleep before you must be active again.
- Call your healthcare provider if your insomnia worsens or is not better within 7 to 10 days. This may mean that there is another condition causing your sleep problem.
- If you take too much SEDATIVE-HYPNOTIC or overdose, call your doctor or poison control center right away, or get emergency treatment.

What are the possible side effects of SEDATIVE-HYPNOTICS?

Serious side effects of SEDATIVE-HYPNOTICS include:

- getting out of bed while not being fully awake and do an activity that you do not know you are doing (See “What is the most important information I should know about SEDATIVE-HYPNOTICS?”)
- abnormal thoughts and behavior. Symptoms include more outgoing or aggressive behavior than normal, confusion, agitation, hallucinations, worsening of depression, and suicidal thoughts or actions.
- memory loss
- anxiety
- severe allergic reactions. Symptoms include swelling of the tongue or throat, trouble breathing, and nausea and vomiting. Get emergency medical help if you get these symptoms after taking SEDATIVE-HYPNOTICS.

Call your doctor right away if you have any of the above side effects or any other side effects that worry you while using the SEDATIVE-HYPNOTIC.

Common side effects of SEDATIVE-HYPNOTICS include:

- drowsiness
- headache
- fatigue
- dizziness
- dry mouth
- upset stomach
- You may still feel drowsy the next day after taking the SEDATIVE-HYPNOTIC. Do not drive or do other dangerous activities after taking the SEDATIVE-HYPNOTIC until you feel fully awake.
- You may have withdrawal symptoms for 1 to 2 days when you stop taking the SEDATIVE-HYPNOTIC. Withdrawal symptoms include trouble sleeping, unpleasant feelings, stomach and muscle cramps, vomiting, sweating, shakiness, and seizures.

These are not all the side effects of SEDATIVE-HYPNOTICS. Ask your doctor or pharmacist for more information. Call your doctor for medical advice about side effects. You may report side effects to FDA at 1-800-FDA-1088.

How should I store SEDATIVE-HYPNOTICS?

- Store SEDATIVE-HYPNOTICS at room temperature between 68° and 77° F (20° to 25°C).
- Keep SEDATIVE-HYPNOTICS and all medicines out of the reach of children.

General information about SEDATIVE-HYPNOTICS

- Medicines are sometimes prescribed for purposes not mentioned in a Medication Guide.
- Do not use the SEDATIVE-HYPNOTIC for a condition for which it was not prescribed.
- Do not give the SEDATIVE-HYPNOTIC to other people, even if they have the same condition. It may harm them and it is against the law.

This Medication Guide summarizes the most important information about SEDATIVE-HYPNOTICS. If you would like more information, talk with your doctor. You can ask you doctor or pharmacist for information about the SEDATIVE-HYPNOTIC that was written for healthcare professionals.

If you would like more information, contact Watson Pharmaceuticals, Inc at 1-800-272-5525.

What are the ingredients in the SEDATIVE-HYPNOTIC?

Active Ingredient: Estazolam

Inactive Ingredients: docusate sodium, lactose monohydrate, magnesium stearate, microcrystalline cellulose, sodium benzoate, sodium starch glycolate and stearic acid. The 2 mg tablets also contain FD&C Red #40 aluminum lake.

Rx only

Manufactured By:
Watson Laboratories, Inc.
Corona, CA 92880 USA

Distributed By:
Watson Pharma, Inc.
Corona, CA 92880 USA

This Medication Guide has been approved by the U.S. Food and Drug Administration.

Repackaged by:

Rebel Distributors Corp

Thousand Oaks, CA 91320

PRINCIPAL DISPLAY PANEL

NDC 21695-220-30
Estazolam
Tablets
2mg
PHARMACIST: PLEASE DISPENSE
WITH ATTACHED MEDICATION GUIDE
30 Tablets Rx only